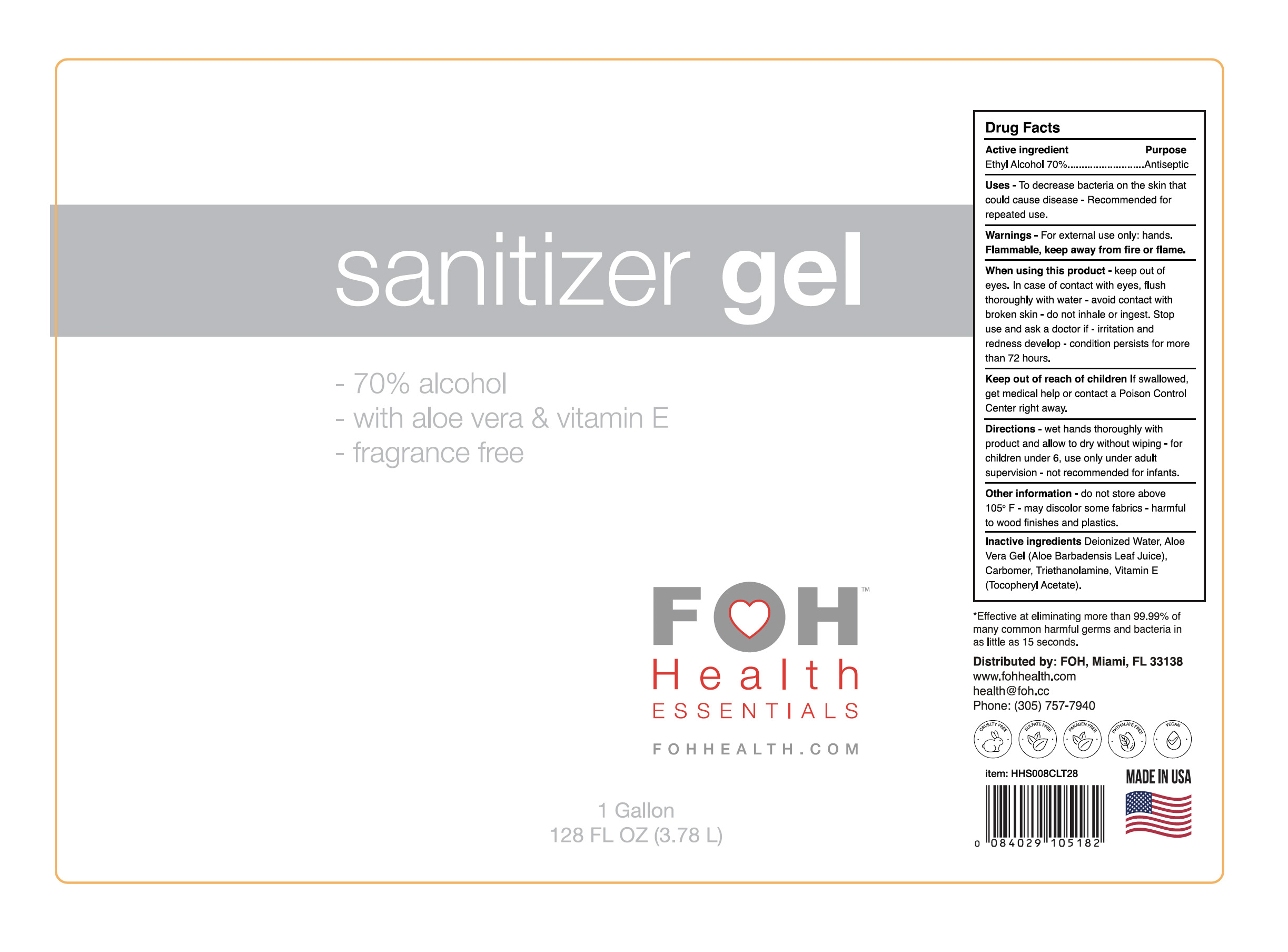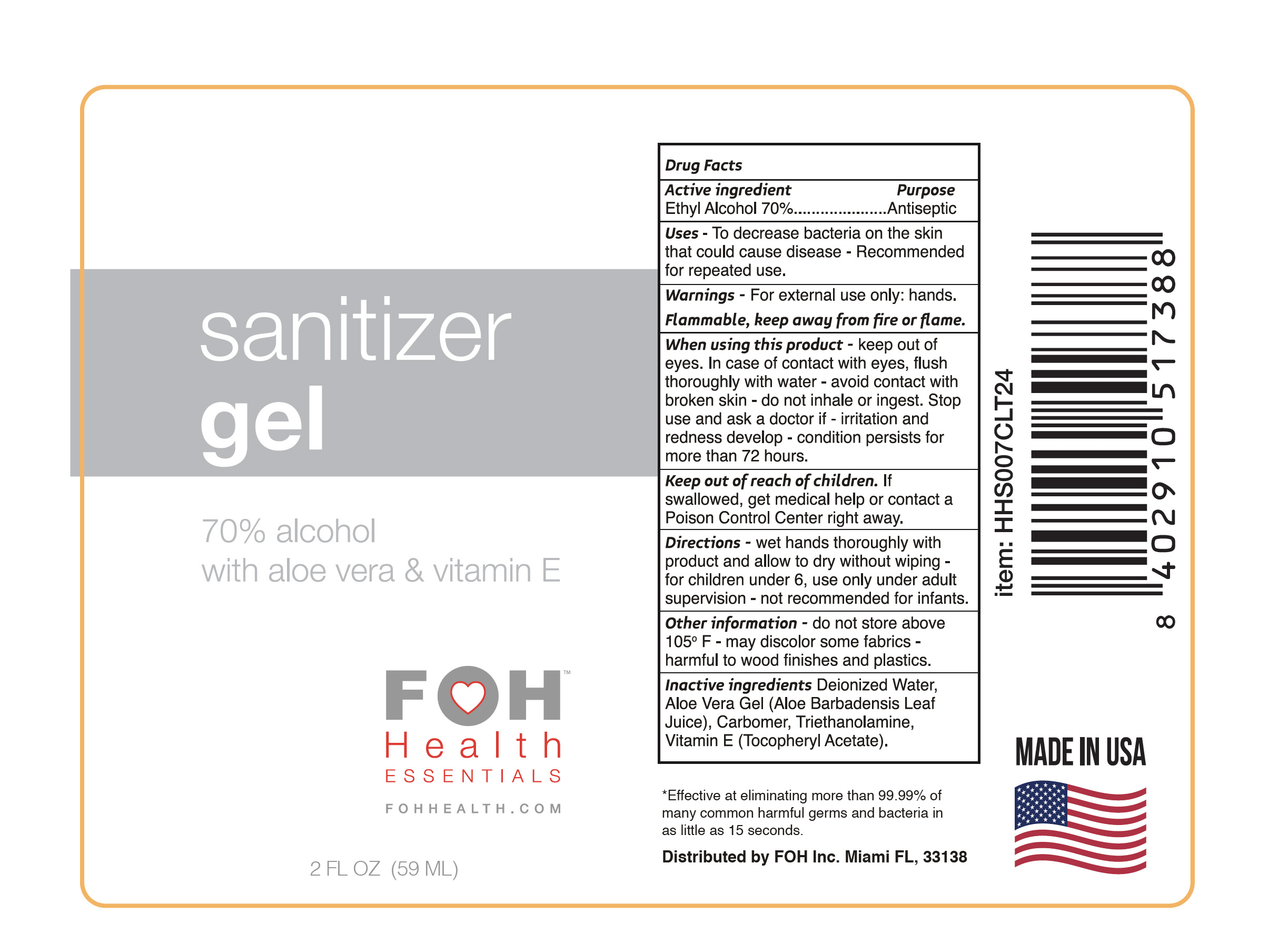 DRUG LABEL: FOH Health Essentials Sanitizer Gel
NDC: 79963-100 | Form: GEL
Manufacturer: FOH INC
Category: otc | Type: HUMAN OTC DRUG LABEL
Date: 20200825

ACTIVE INGREDIENTS: ALCOHOL 70 mL/100 mL
INACTIVE INGREDIENTS: WATER; ALOE VERA LEAF; CARBOMER HOMOPOLYMER, UNSPECIFIED TYPE; TROLAMINE; .ALPHA.-TOCOPHEROL ACETATE

Packaging

Warnings

For external use only: hands.

FLAMMABLE, KEEP AWAY FROM FIRE OR FLAME.
When using this product ▪ Keep out of eyes. In case of contact with eyes, flush thoroughly with water
▪ Avoid contact with broken skin ▪ Do not inhale or ingest ▪ Stop use and ask a doctor if: irritation and
redness develop or condition persists for more than 72 hours

Active Ingredient

Ethyl alcohol 70%

Purpose

Antiseptic

Keep out of reach of children

If swallowed, get medical help or contact a Poison Control Center right
away

Uses

To decrease bacteria on the skin that could cause disease ▪ Recommended for repeated use

Inactive Ingredients

Deionized Water, Aloe Vera Gel (Aloe Barbadensis Leaf Juice), Carbomer,
Triethanolamine, Vitamin E (Tocopheryl Acetate).

Directions

Wet hands thoroughly with product and allow to dry without wiping ▪ For children under 6,
use only under adult supervision ▪ Not recommended for infants.

Other Information

Do not store above 105°F ▪ May discolor some fabrics ▪ Harmful to wood finishes and plastics.

70% ALCOHOL
Kills 99.99% of Germs
Aloe Vera & Vitamin E
Fragrance Free

*Effective at eliminating more than 99.99% of many common harmful germs and bacteria in as little as 15 seconds.

Distributed by: FOH Inc Miami, FL 33138
fohhealth.com

CRUELTY FREE
VEGAN
PARABEN FREE
NO SULFATES
MADE IN USA